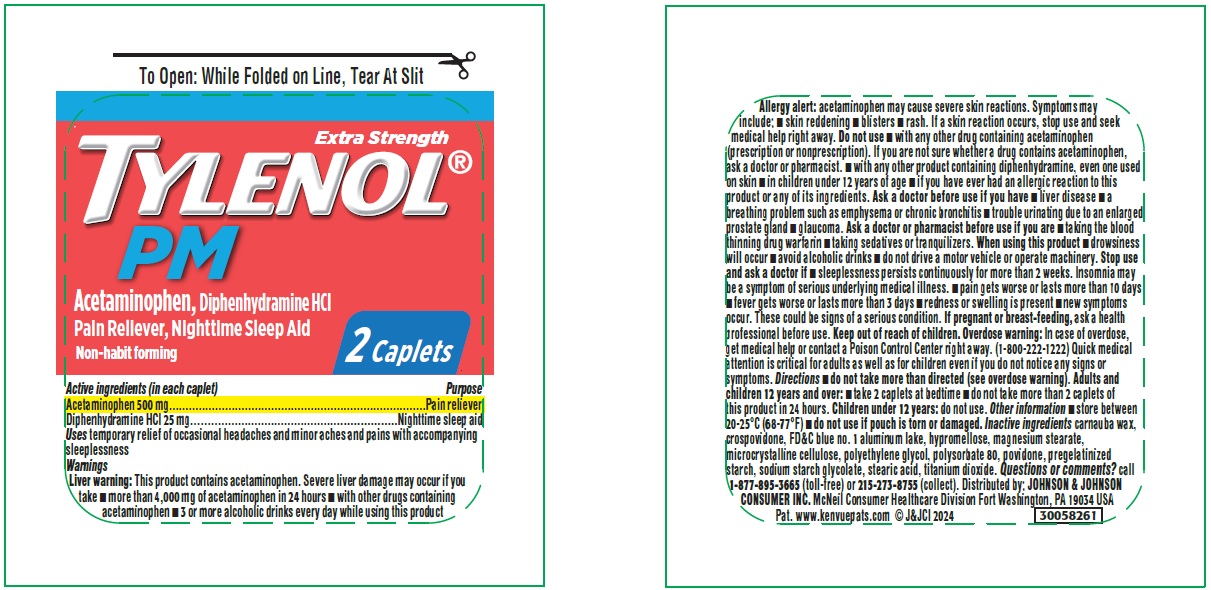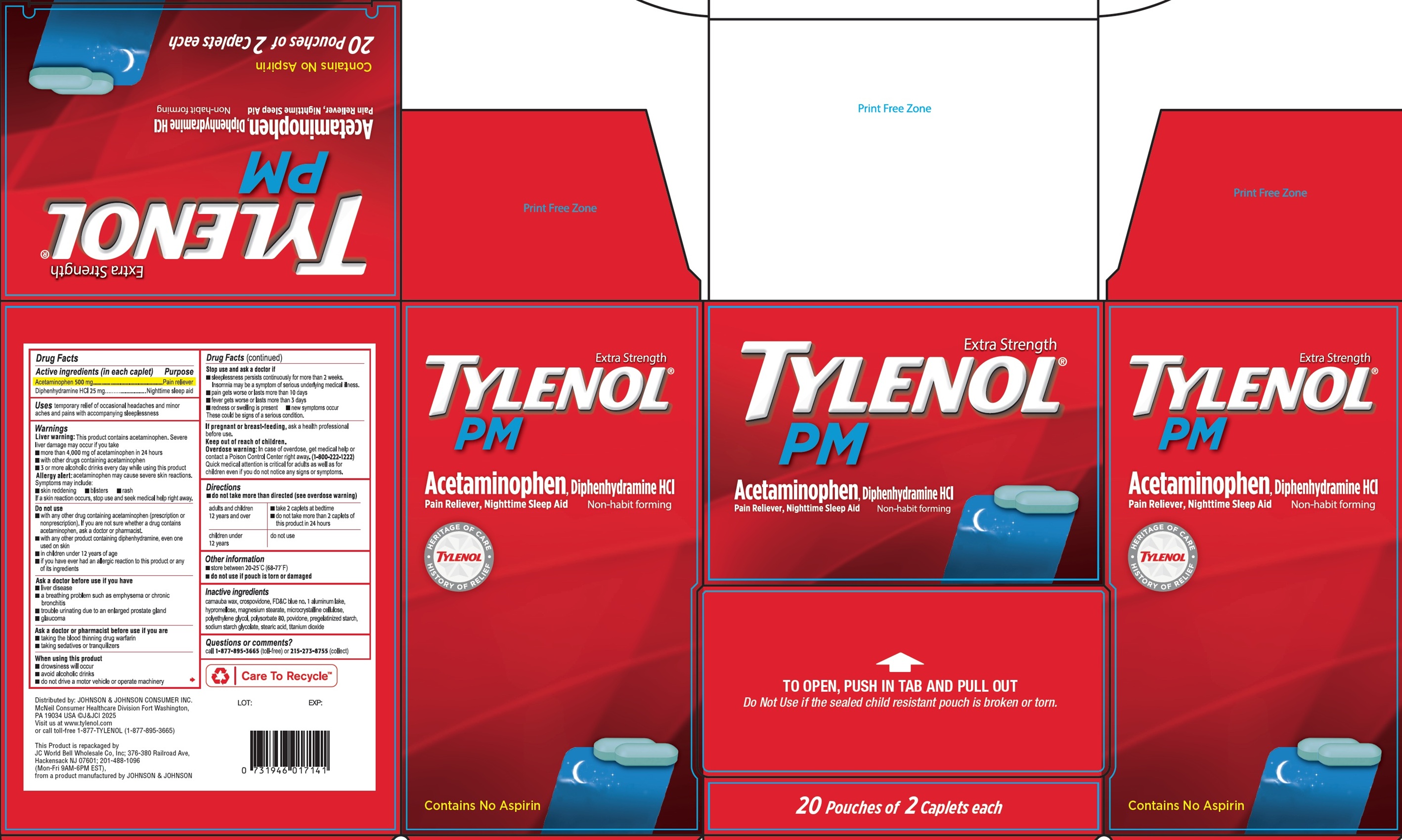 DRUG LABEL: Tylenol PM
NDC: 50269-552 | Form: TABLET, FILM COATED
Manufacturer: JC World Bell Wholesale Co., Inc.
Category: otc | Type: HUMAN OTC DRUG LABEL
Date: 20260106

ACTIVE INGREDIENTS: ACETAMINOPHEN 500 mg/1 1; DIPHENHYDRAMINE HYDROCHLORIDE 25 mg/1 1
INACTIVE INGREDIENTS: CARNAUBA WAX; CROSPOVIDONE; FD&C BLUE NO. 1 ALUMINUM LAKE; HYPROMELLOSE, UNSPECIFIED; MAGNESIUM STEARATE; MICROCRYSTALLINE CELLULOSE; POLYETHYLENE GLYCOL, UNSPECIFIED; POLYSORBATE 80; POVIDONE; SODIUM STARCH GLYCOLATE TYPE A; STEARIC ACID; TITANIUM DIOXIDE

Tylenol PM

Active ingredients (in each caplet)

Acetaminophen 500 mg
Diphenhydramine HCl 25 mg

Purpose

Pain reliever

Nighttime sleep aid

Uses

temporary relief of occasional headaches and minor aches and pains with accompanying sleeplessness

Warnings

Liver warning:This product contains acetaminophen. Severe liver damage may occur if you take

- more than 4,000 mg of acetaminophen in 24 hours
- with other drugs containing acetaminophen
- 3 or more alcoholic drinks every day while using this product
  Allergy alert:acetaminophen may cause severe skin reactions. Symptoms may include:
  • skin reddening • blisters • rash
  If a skin reactions occurs, stop use and seek medical help right away.

Do not use

- with any other drug containing acetaminophen (prescription or nonprescription). If you are not sure whether a drug contains acetaminophen, ask a doctor or pharmacist.
- with any other product containing diphenhydramine, even one used on skin
- in children under 12 years of age
- if you have ever had an allergic reaction to this product or any of its ingredients

Ask a doctor before use if you have

- liver disease
- a breathing problem such as emphysema or chronic bronchitis
- trouble urinating due to an enlarged prostate gland
- glaucoma

Ask a doctor or pharmacist before use if you are

- taking the blood thinning drug warfarin
- taking sedatives or tranquilizers

When using this product

- drowsiness will occur
- avoid alcoholic drinks
- do not drive a motor vehicle or operate machinery

Stop use and ask a doctor if

- sleeplessness persists continuously for more than 2 weeks. Insomnia may be a symptom of serious underlying medical illness.
- pain gets worse or lasts more than 10 days
- fever gets worse or lasts more than 3 days
- redness or swelling is present
- new symptoms occur

These could be signs of a serious condition.

If pregnant or breast-feeding,

ask a health professional before use.

Keep out of reach of children.

Overdose warning:In case of overdose, get medical helo or contact a Posion Control Center right away. (1-800-222-1222) Quick medical attention is critical for adults as well as for children even if you do not notice any signs or symptoms.

Directions

- do not take more than directed (see overdose warning)

adults and children 12 years and over | - take 2 caplets at bedtime - do not take more than 2 caplets of this product in 24 hours
children under 12 years | do not use

Other information

- store between 20-25°C (68-77°F)
- do not use if pouch is torn or damaged

Inactive ingredients

carnauba wax, crospovidone, FD&C blue no. 1 aluminum lake, hypromellose, magnesium stearate, microcrystalline cellulose, polyethylene glycol, polysorbate 80, povidone, pregelatinized starch, sodium starch glycolate, stearic acid, titanium dioxide

Questions or comments?

call 1-877-895-3665(toll-free) or 215-273-8755(collect)